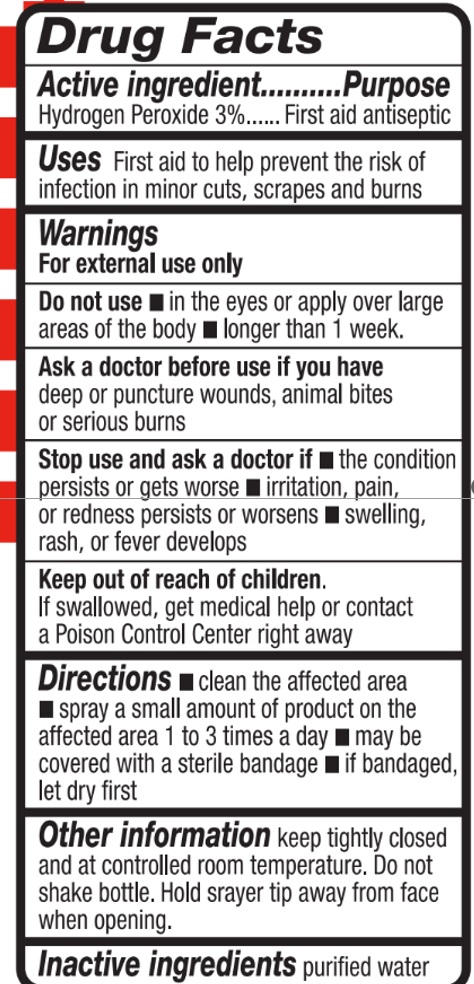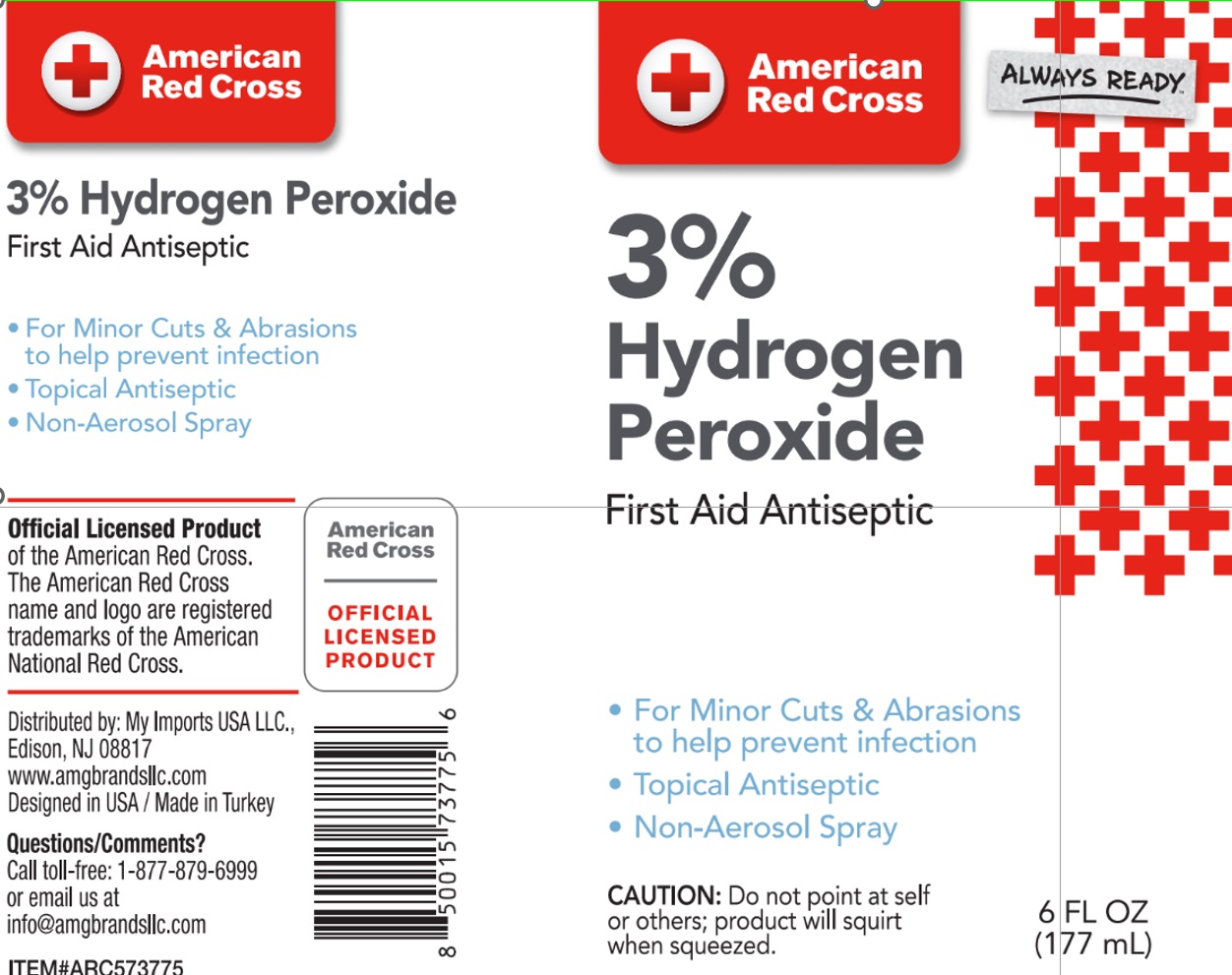 DRUG LABEL: American Red Cross 6oz, 3% Hydrogen Peroxide
NDC: 51628-3775 | Form: SPRAY
Manufacturer: MY IMPORTS USA LLC
Category: otc | Type: HUMAN OTC DRUG LABEL
Date: 20241213

ACTIVE INGREDIENTS: HYDROGEN PEROXIDE 5.31 mL/177 mL
INACTIVE INGREDIENTS: AQUA 171.69 mL/177 mL

AMERICAN RED CROSS HYDROGEN PEROXIDE 3%

ACTIVE INGREDIENT

Active Ingredient ..... purpose

Hydrogen Peroxide 3% .... first aid anticeptic

Ask a doctor before use if you have deep or puncture wounds, animal bites or serious burns

Do not use in the eyes or apply over large areas of the body

longer than 1 week

Keep out of reach of children

If swallowed, get medical help or contact a Poison Control Center right away

USES

First aid to help prevent the risk of infection in minor cuts, scrapes and burns

STOP USE

Stop use and ask a doctor if the condition persists or gets worse

irritation, pain or redness persists or worsens

swelling, rash or fever develops

OTHER INFORMATION

keep tightly closed and at controlled room temperature

do not shake the bottle

hold sprayer tip away from face when opening

INACTIVE INGREDIENTS

purified water

DIRECTIONS

clean the affected area

spray a small amount of product on the affected area 1 to 3 times a day

may be covered with a sterile bandage

if bandaged, let it dry first

DIRECTIONS

clean the affected area

spray a small amount of product on the affected area 1 to 3 times a day

may be covered with a sterile bandage

if bandaged, let dry first

WARNINGS

For external use only